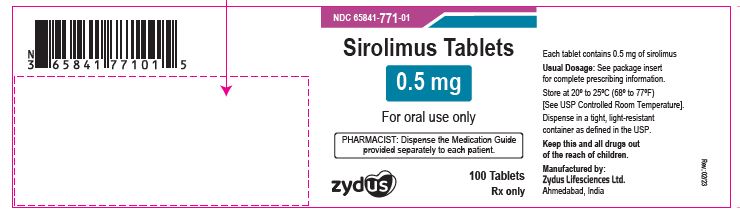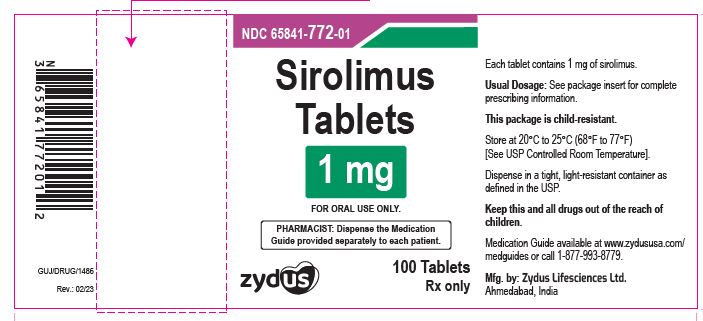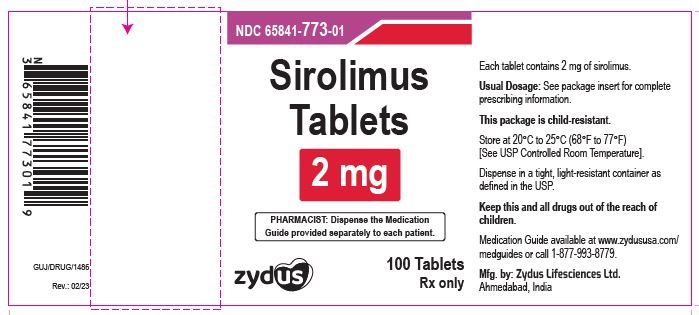 DRUG LABEL: sirolimus
NDC: 65841-771 | Form: TABLET, FILM COATED
Manufacturer: Zydus Lifesciences Limited
Category: prescription | Type: HUMAN PRESCRIPTION DRUG LABEL
Date: 20230927

ACTIVE INGREDIENTS: SIROLIMUS 0.5 mg/1 1
INACTIVE INGREDIENTS: ALPHA-TOCOPHEROL ACETATE; CELLULOSE, MICROCRYSTALLINE; CITRIC ACID MONOHYDRATE; CROSPOVIDONE (15 MPA.S AT 5%); FD&C YELLOW NO. 5; FERRIC OXIDE YELLOW; GLYCERYL OLEATE; HYPROMELLOSES; LACTOSE MONOHYDRATE; POLOXAMER 188; POLYETHYLENE GLYCOL, UNSPECIFIED; POVIDONE; SUCROSE; TALC; TITANIUM DIOXIDE

SIROLIMUS TABLETS

PACKAGE LABEL.PRINCIPAL DISPLAY PANEL

Sirolimus Tablets, 0.5 mg

NDC 65841-771-01

100 Tablets

Rx only

Sirolimus Tablets, 1 mg

NDC 65841-772-01

100 Tablets

Rx only

Sirolimus Tablets, 2 mg

NDC 65841-773-01

100 Tablets

Rx only